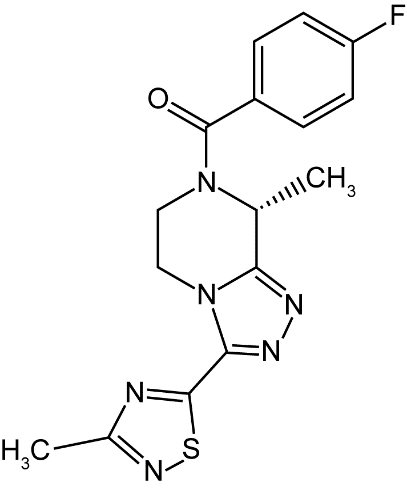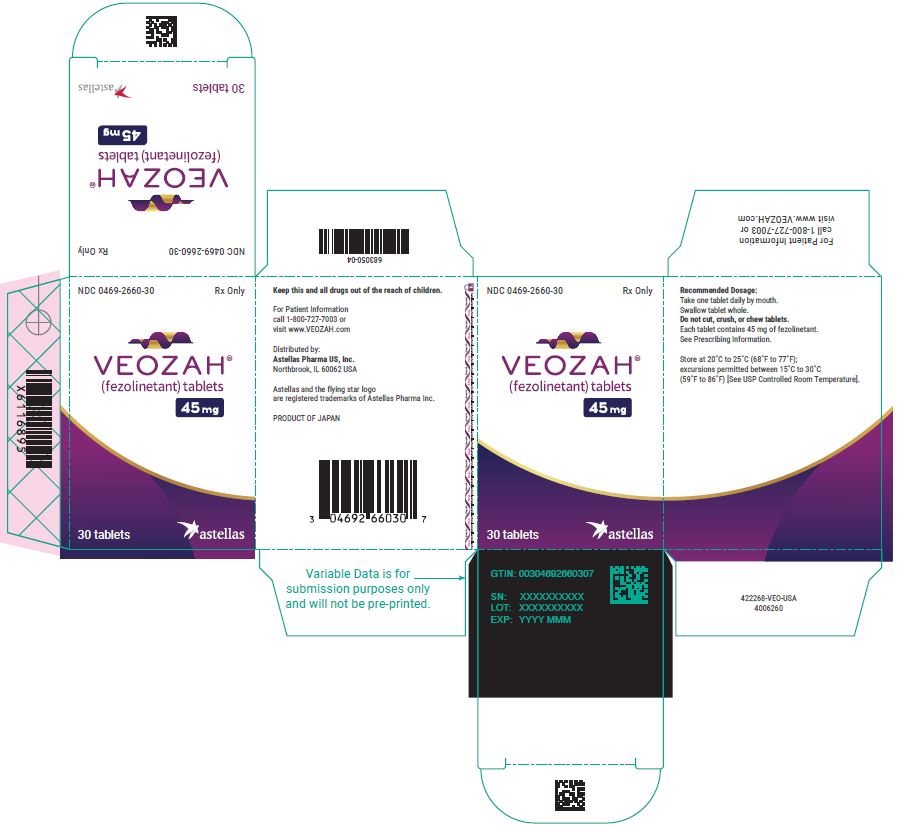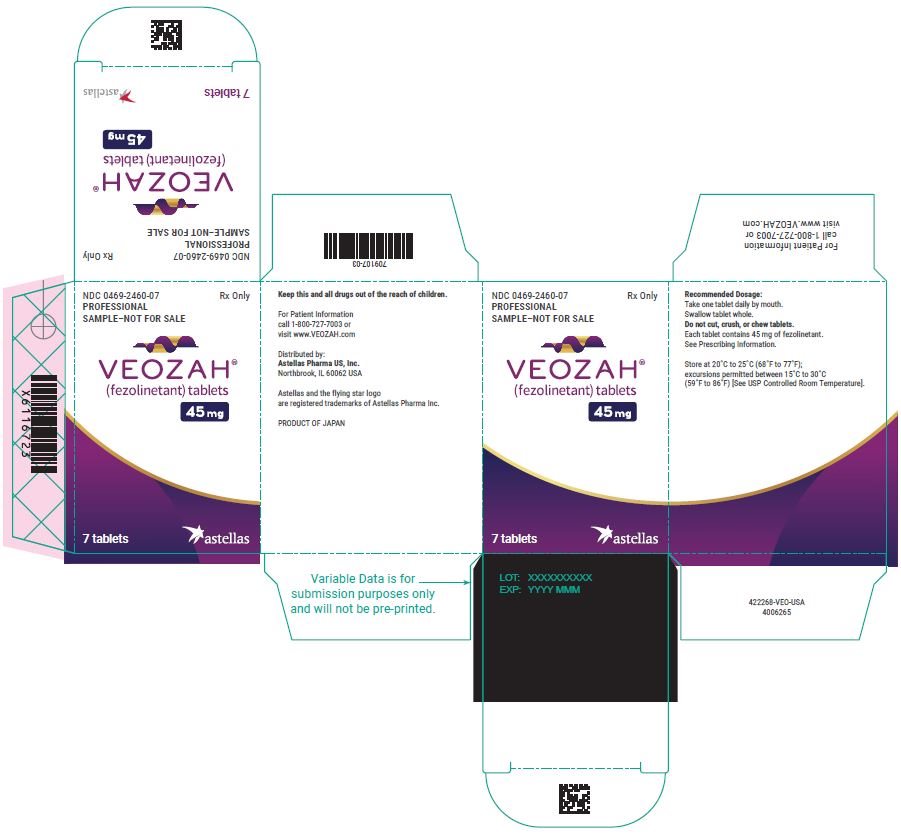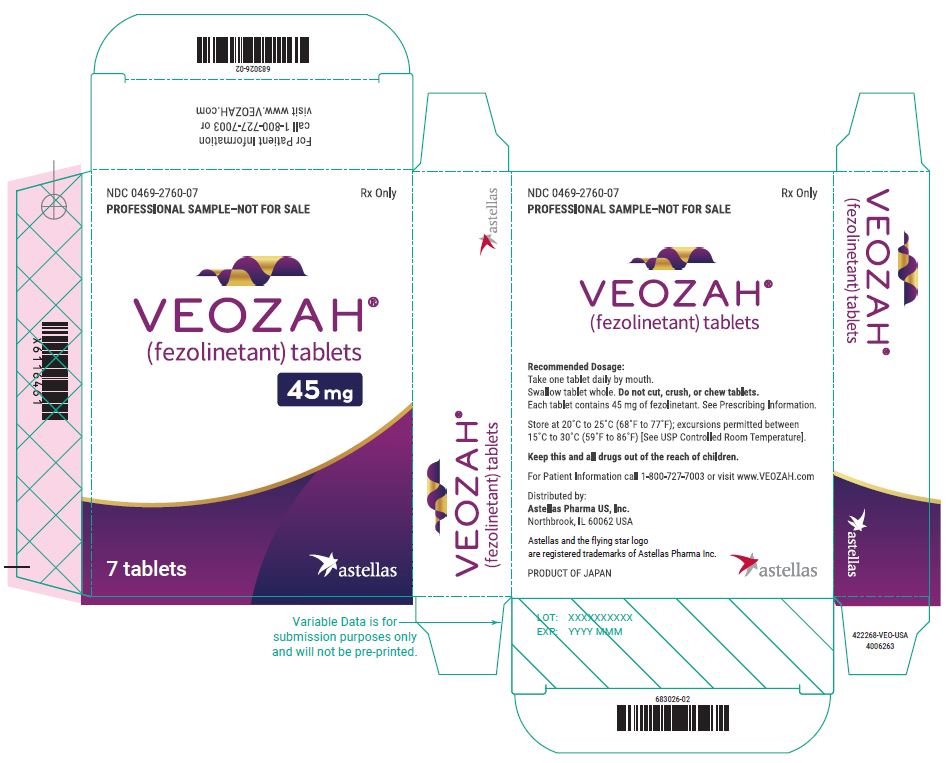 DRUG LABEL: VEOZAH
NDC: 0469-2660 | Form: TABLET, FILM COATED
Manufacturer: Astellas Pharma US, Inc.
Category: prescription | Type: HUMAN PRESCRIPTION DRUG LABEL
Date: 20241227

ACTIVE INGREDIENTS: FEZOLINETANT 45 mg/1 1
INACTIVE INGREDIENTS: MANNITOL; HYDROXYPROPYL CELLULOSE, UNSPECIFIED; LOW-SUBSTITUTED HYDROXYPROPYL CELLULOSE, UNSPECIFIED; MICROCRYSTALLINE CELLULOSE; MAGNESIUM STEARATE; HYPROMELLOSE 2910 (6 MPA.S); TALC; POLYETHYLENE GLYCOL 8000; TITANIUM DIOXIDE; FERRIC OXIDE RED

HIGHLIGHTS OF PRESCRIBING INFORMATION

These highlights do not include all the information needed to use VEOZAH safely and effectively. See full prescribing information for VEOZAH.
VEOZAH® (fezolinetant) tablets, for oral use
Initial U.S. Approval: 2023

WARNING: RISKS OF HEPATOTOXICITY

See full prescribing information for complete boxed warning.

Hepatotoxicity has occurred with the use of VEOZAH in the postmarketing setting (5.1).

- Perform hepatic laboratory tests prior to initiation of treatment to evaluate for hepatic function and injury. Do not start VEOZAH if either aminotransferase is ≥ 2 x ULN or if the total bilirubin is ≥ 2 x ULN for the evaluating laboratory.
- Perform follow-up hepatic laboratory testing monthly for the first 3 months, at 6 months, and 9 months of treatment (2.1, 5.1).
- Advise patients to discontinue VEOZAH immediately and seek medical attention including hepatic laboratory tests if they experience signs or symptoms that may suggest liver injury (new onset fatigue, decreased appetite, nausea, vomiting, pruritus, jaundice, pale feces, dark urine, or abdominal pain) (2.1, 5.1).
- Discontinue VEOZAH if transaminase elevations are > 5 x ULN, or if transaminase elevations are > 3 x ULN and the total bilirubin level is > 2 x ULN.
- If transaminase elevations > 3 x ULN occur, perform more frequent follow-up hepatic laboratory tests until resolution (5.1).

RECENT MAJOR CHANGES

Boxed Warning, Hepatotoxicity | 12/2024
Dosage and Administration, Recommended Dosage (2.1) | 12/2024
Warnings and Precautions, Hepatotoxicity (5.1) | 12/2024

1 INDICATIONS AND USAGE

VEOZAH is a neurokinin 3 (NK3) receptor antagonist indicated for the treatment of moderate to severe vasomotor symptoms due to menopause. (1)

2 DOSAGE AND ADMINISTRATION

One 45 mg tablet orally once daily with or without food.

Perform baseline hepatic laboratory tests to evaluate for hepatic function and injury before beginning VEOZAH. While using VEOZAH, perform follow-up hepatic laboratory tests monthly for the first 3 months, at 6 months, and 9 months after initiation of therapy or when signs or symptoms suggest liver injury. (2.1)

3 DOSAGE FORMS AND STRENGTHS

Tablets: 45 mg (3)

4 CONTRAINDICATIONS

- Known cirrhosis (4, 5.1)
- Severe renal impairment or end-stage renal disease (4, 8.6)
- Concomitant use with CYP1A2 inhibitors (4, 7.1)

5 WARNINGS AND PRECAUTIONS

Hepatotoxicity: Cases of hepatotoxicity and jaundice have been reported in the postmarketing setting. Perform hepatic laboratory tests prior to initiation of VEOZAH to evaluate for hepatic function and injury. Perform follow-up hepatic laboratory tests monthly for the first 3 months, at 6 months, and 9 months after initiation of therapy.

Advise patients to discontinue VEOZAH immediately and seek medical attention including hepatic laboratory tests if they experience signs or symptoms that may suggest liver injury (new onset fatigue, decreased appetite, nausea, vomiting, pruritus, jaundice, pale feces, dark urine, or abdominal pain). (5.1)

6 ADVERSE REACTIONS

The most common adverse reactions with VEOZAH [at least 2% in VEOZAH 45 mg and greater than placebo] are: abdominal pain, diarrhea, insomnia, back pain, hot flush, and hepatic transaminase elevation. (6.1)

To report SUSPECTED ADVERSE REACTIONS, contact Astellas Pharma US, Inc. at 1-800-727-7003 or FDA at 1-800-FDA-1088 or www.fda.gov/medwatch.

FULL PRESCRIBING INFORMATION

WARNING: RISKS OF HEPATOTOXICITY

Hepatotoxicity has occurred with the use of VEOZAH in the postmarketing setting (5.1).

- Perform hepatic laboratory tests prior to initiation of treatment to evaluate for hepatic function and injury. Do not start VEOZAH if either aminotransferase is ≥ 2 x the upper limit of normal (ULN) or if the total bilirubin is ≥ 2 x ULN for the evaluating laboratory.
- Perform follow-up hepatic laboratory testing monthly for the first 3 months, at 6 months, and 9 months of treatment (2.1, 5.1).
- Advise patients to discontinue VEOZAH immediately and seek medical attention including hepatic laboratory tests if they experience signs or symptoms that may suggest liver injury (new onset fatigue, decreased appetite, nausea, vomiting, pruritus, jaundice, pale feces, dark urine, or abdominal pain) (2.1, 5.1).
- Discontinue VEOZAH if transaminase elevations are > 5 x ULN, or if transaminase elevations are > 3 x ULN and the total bilirubin level is > 2 x ULN.
- If transaminase elevations > 3 x ULN occur, perform more frequent follow-up hepatic laboratory tests until resolution (5.1).

1 INDICATIONS AND USAGE

VEOZAH® is indicated for the treatment of moderate to severe vasomotor symptoms due to menopause.

2 DOSAGE AND ADMINISTRATION

2.1 Recommended Dosage

Take a single 45 mg VEOZAH tablet orally once daily with or without food.

Take VEOZAH with liquids and swallow whole. Do not cut, crush, or chew tablets.

Administer VEOZAH orally at about the same time each day. If a dose of VEOZAH is missed or not taken at the usual time, administer the missed dose as soon as possible, unless there is less than 12 hours before the next scheduled dose. Return to the regular schedule the following day.

Perform baseline hepatic laboratory tests to evaluate for hepatic function and injury [including serum alanine aminotransferase (ALT), serum aspartate aminotransferase (AST), serum alkaline phosphatase (ALP), and serum bilirubin (total and direct)] before initiating treatment with VEOZAH. Do not start VEOZAH if ALT or AST is ≥ 2 x ULN or if the total bilirubin is ≥ 2 x ULN for the evaluating laboratory.

While using VEOZAH, perform follow-up hepatic laboratory tests monthly for the first 3 months, at 6 months, and 9 months after initiation of therapy.

Advise patients to discontinue VEOZAH immediately and seek medical attention including hepatic laboratory tests if they experience signs or symptoms that may suggest liver injury [see Warnings and Precautions (5.1)].

3 DOSAGE FORMS AND STRENGTHS

Tablets: 45 mg, round, light red, film-coated tablets, debossed with the Astellas logo and ‘645’ on the same side.

4 CONTRAINDICATIONS

VEOZAH is contraindicated in women with any of the following conditions:

- Known cirrhosis [see Warnings and Precautions (5.1), Use in Specific Populations (8.7), and Clinical Pharmacology (12.3)].
- Severe renal impairment or end-stage renal disease [see Use in Specific Populations (8.6) and Clinical Pharmacology (12.3)].
- Concomitant use with CYP1A2 inhibitors [see Drug Interactions (7.1) and Clinical Pharmacology (12.3)].

5 WARNINGS AND PRECAUTIONS

5.1 Hepatotoxicity

In three clinical trials, elevations in serum transaminase [alanine aminotransferase (ALT) and/or aspartate aminotransferase (AST)] levels > 3 x the upper limit of normal (ULN) occurred in 2.3% [exposure adjusted incidence rate (EAIR) of 2.7 per 100 person-years] of women receiving VEOZAH and 0.9% (EAIR of 1.5 per 100 person-years) of women receiving placebo. No elevations in serum total bilirubin (> 2 x ULN) occurred. Women with ALT or AST elevations were generally asymptomatic. Transaminase levels returned to pretreatment levels (or close to these) without sequelae with dose continuation, and upon dose interruption, or discontinuation. Women with cirrhosis were not studied [see Adverse Reactions (6.1)].

In the postmarketing setting, cases of drug-induced liver injury with elevations of ALT, AST, alkaline phosphatase (ALP), and total bilirubin occurred within 40 days of starting VEOZAH. Patients reported a general sense of feeling unwell and symptoms of fatigue, nausea, pruritus, jaundice, pale feces, and dark urine. The patients’ signs and symptoms gradually resolved after discontinuation of VEOZAH [see Adverse Reactions (6.2)].

Perform baseline hepatic laboratory tests to evaluate for hepatic function and injury [including serum ALT, serum AST, serum ALP, and serum bilirubin (total and direct)] prior to VEOZAH initiation. Do not start VEOZAH if ALT or AST is ≥ 2 x ULN or if the total bilirubin is ≥ 2 x ULN for the evaluating laboratory.

Perform follow-up hepatic laboratory tests monthly for the first 3 months, at 6 months, and 9 months after initiation of therapy.

Advise patients to discontinue VEOZAH immediately and seek medical attention including hepatic laboratory tests if they experience signs or symptoms that may suggest liver injury:

- new onset fatigue, decreased appetite, nausea, vomiting, pruritus, jaundice, pale feces, dark urine, or abdominal pain.

Discontinue VEOZAH if:

- transaminase elevations are > 5 x ULN.
- transaminase elevations are > 3 x ULN and total bilirubin is > 2 x ULN.

If transaminase elevations > 3 x ULN occur, perform more frequent follow-up hepatic laboratory tests until resolution.

Exclude alternative causes of hepatic laboratory test elevations.

6 ADVERSE REACTIONS

The following serious adverse reactions are discussed elsewhere in the labeling:

- Hepatic Transaminase Elevation and Hepatotoxicity [see Warnings and Precautions (5.1)].

6.1 Clinical Trials Experience

Because clinical trials are conducted under widely varying conditions, adverse reaction rates observed in the clinical trials of a drug cannot be directly compared to rates in the clinical trials of another drug and may not reflect the rates observed in clinical practice.

The safety of VEOZAH was evaluated in three 52-week clinical trials [see Clinical Studies (14)]. Across the three clinical trials, a total of 1100 women received VEOZAH. Trials 1 and 2 were placebo-controlled for the first 12 weeks, followed by re-randomization of women previously receiving placebo to VEOZAH (women on VEOZAH remained on VEOZAH) for an additional 40 weeks of uncontrolled treatment. Trial 3 was a randomized, placebo-controlled, double-blind safety study evaluating the safety of VEOZAH for 52 weeks. The adverse reactions reported in at least 2% in VEOZAH 45 mg and greater than placebo in Trial 3 are presented in Table 1.

Table 1: Adverse Reactions Reported in at Least 2% in VEOZAH 45 mg and Greater Than Placebo in a Placebo-Controlled, Double-Blind 52-Week Trial (Trial 3)
Adverse Reaction | VEOZAH 45 mg; (n=609); Total Person-Years=504.2; n (%, EAIR [EAIR = Number of individuals experiencing an adverse event divided by exposure time (total person-years) x 100.]) | Placebo; (n=610); Total Person-Years=475.0; n (%, EAIR)
Abdominal pain [Abdominal pain (including Abdominal pain, Abdominal pain lower, Abdominal pain upper).] | 26 (4.3%, 5.2) | 13 (2.1%, 2.7)
Diarrhea | 24 (3.9%, 4.8) | 16 (2.6%, 3.4)
Insomnia | 24 (3.9%, 4.8) | 11 (1.8%, 2.3)
Back pain | 18 (3.0%, 3.6) | 13 (2.1%, 2.7)
Hot flush | 15 (2.5%, 3.0) | 10 (1.6%, 2.1)
Hepatic transaminase elevation [Hepatic transaminase elevations (including Alanine aminotransferase abnormal, Alanine aminotransferase increased, Aspartate aminotransferase abnormal, Aspartate aminotransferase increased).] | 14 (2.3%, 2.8) | 5 (0.8%, 1.1)

In the pooled laboratory data of Trials 1, 2, and 3, elevated hepatic transaminases (> 3 x ULN) occurred in 25 women (2.3%, 2.7 EAIR) exposed to VEOZAH 45 mg (n=1100, 912.1 total person-years) as compared to 8 women (0.9%, 1.5 EAIR) exposed to placebo (n=952, 549.1 total person-years).

6.2 Postmarketing Experience

The following adverse reactions have been identified during postapproval use of VEOZAH. Because these reactions are reported voluntarily from a population of uncertain size, it is not always possible to reliably estimate their frequency or establish a causal relationship to drug exposure.

Hepatic: Cases of serious drug-induced hepatotoxicity occurred within 40 days of starting VEOZAH. Patients experienced elevated transaminases (up to 50 x ULN at peak elevation), elevated alkaline phosphatase (up to 4 x ULN at peak elevation), and bilirubin (up to 5 x ULN at peak elevation) coupled with symptoms of fatigue, nausea, pruritus, jaundice, pale feces, and dark urine. After discontinuation of VEOZAH, these abnormalities gradually resolved.

7 DRUG INTERACTIONS

7.1 Effect of Other Drugs on VEOZAH

CYP1A2 Inhibitors

VEOZAH is a substrate of CYP1A2. Concomitant use of VEOZAH with drugs that are weak, moderate, or strong CYP1A2 inhibitors, increase the plasma Cmax and AUC of VEOZAH [see Clinical Pharmacology (12.3)].

VEOZAH is contraindicated in individuals using CYP1A2 inhibitors.

8 USE IN SPECIFIC POPULATIONS

8.1 Pregnancy

Risk Summary

There are no data on VEOZAH use in pregnant women to evaluate for a drug-associated risk of major birth defects, miscarriage, or adverse maternal or fetal outcomes.

In embryo-fetal toxicity animal studies with fezolinetant, embryo-lethality occurred at high doses above the human therapeutic dose in rats and rabbits, but no teratogenicity was observed. In the pre- and post-natal development animal study, delayed parturition and embryo-lethality occurred at high doses above the human therapeutic dose in rats. Additionally, in the male offspring delayed male reproductive maturation was observed, characterized by incomplete preputial separation, which affected male fertility at doses above the human therapeutic dose in rats [see Data].

In the U.S. general population, the estimated background risk of major birth defects or miscarriage in clinically recognized pregnancies are 2-4% and 15-20%, respectively.

Data

Animal Data

In embryo-fetal development toxicity studies in rats and rabbits, embryo-lethality was noted at the highest doses (128- and 174-fold the human AUC24 at the human therapeutic dose for rats and rabbits, respectively). The no observed adverse effect level (NOAEL) for embryo-fetal development was 50 mg/kg/day in rats and 45 mg/kg/day in rabbits (62- and 16‑fold the human AUC24 at the human therapeutic dose for rats and rabbits, respectively). Fezolinetant showed no effects on fertility and early embryonic development in rats [see Nonclinical Toxicology (13.1)].

In the pre- and post-natal development study in rats, the NOAEL for maternal and fetal toxicity was 30 mg/kg/day (36‑fold the human AUC24 at the human therapeutic dose) based on delayed parturition and embryo-lethality at 100 mg/kg/day. The NOAEL for F1 generation development was determined to be 100 mg/kg/day for females (204-fold the human AUC24 at the human therapeutic dose) and 10 mg/kg/day for males (11-fold the human AUC24 at the human therapeutic dose). The F1 male showed delayed male reproductive maturation, characterized as incomplete balanopreputial separation at time of mating, at doses of greater than or equal to 30 mg/kg/day (36-fold the human AUC24 at the human therapeutic dose), which affected male fertility [see Nonclinical Toxicology (13.1)].

8.2 Lactation

Risk Summary

There are no data on the presence of fezolinetant in human milk, the effects on the breastfed child, or the effects on milk production. It is not known if fezolinetant is present in human milk.

Data

Animal Data

Following administration of radiolabeled fezolinetant to lactating rats, the radioactivity concentration in milk was higher than that in the plasma at all time points, indicating that fezolinetant-derived components transferred to the tissues in infant rats via breast milk.

8.4 Pediatric Use

The efficacy and safety of VEOZAH in individuals less than 18 years of age have not been established.

8.5 Geriatric Use

There have not been sufficient numbers of geriatric women involved in clinical trials utilizing VEOZAH to determine whether those over 65 years of age differ from younger women in their response to VEOZAH.

8.6 Renal Impairment

VEOZAH is contraindicated in individuals with severe (eGFR 15 to less than 30 mL/min/1.73 m^2) renal impairment or end-stage renal disease (eGFR less than 15 mL/min/1.73 m^2) [see Clinical Pharmacology (12.3)]. No dose adjustment of VEOZAH is recommended for individuals with mild (eGFR 60 to less than 90 mL/min/1.73 m^2) or moderate (eGFR 30 to less than 60 mL/min/1.73 m^2) renal impairment.

8.7 Hepatic Impairment

Child-Pugh Class A or B hepatic impairment increased the exposure of VEOZAH [see Clinical Pharmacology (12.3)]. VEOZAH has not been studied in individuals with Child-Pugh Class C hepatic impairment.

VEOZAH is contraindicated in individuals with cirrhosis [see Clinical Pharmacology (12.3)].

10 OVERDOSAGE

Treatment of overdose consists of discontinuation of VEOZAH therapy with institution of appropriate symptomatic care.

11 DESCRIPTION

VEOZAH (fezolinetant) is a small-molecule NK3 receptor antagonist.

The chemical name of fezolinetant is (4-Fluorophenyl)[(8R)-8-methyl-3-(3-methyl-1,2,4-thiadiazol-5-yl)-5,6-dihydro[1,2,4]triazolo[4,3-a]pyrazin-7(8H)-yl]methanone having a molecular formula of C16H15FN6OS and a molecular weight of 358.39. The structural formula of fezolinetant is:

Fezolinetant is a white powder. It is very slightly soluble in water (0.29 mg/mL).

Each VEOZAH (fezolinetant) tablet for oral use contains 45 mg of fezolinetant and the following inactive ingredients: ferric oxide, hydroxypropyl cellulose, hypromellose, low-substituted hydroxypropyl cellulose, magnesium stearate, mannitol, microcrystalline cellulose, polyethylene glycol, talc, and titanium dioxide.

12 CLINICAL PHARMACOLOGY

12.1 Mechanism of Action

VEOZAH is a neurokinin 3 (NK3) receptor antagonist that blocks neurokinin B (NKB) binding on the kisspeptin/neurokinin B/dynorphin (KNDy) neuron to modulate neuronal activity in the thermoregulatory center. Fezolinetant has high affinity for the NK3 receptor (Ki value of 19.9 to 22.1 nmol/L), which is more than 450-fold higher than binding affinity to NK1 or NK2 receptors.

12.2 Pharmacodynamics

Treatment with fezolinetant did not show any clear trends in sex hormones measured (follicle-stimulating hormone, testosterone, estrogen, and dehydroepiandrosterone sulfate) in menopausal women. Transient decrease of luteinizing hormone (LH) levels was observed at peak concentrations of fezolinetant.

Cardiac Electrophysiology

At a dose 20 times the maximum approved recommended dose, fezolinetant does not prolong the QT interval to any clinically relevant extent.

12.3 Pharmacokinetics

In healthy women, fezolinetant Cmax and AUC increased proportionally over a dosage range from 20 to 60 mg once daily (0.44 to 1.33 times the approved recommended dosage).

Steady-state plasma concentrations of fezolinetant were reached after two once daily doses, with minimal fezolinetant accumulation.

Absorption

The median (range) time to reach fezolinetant Cmax is 1.5 (1 to 4) hours in healthy women.

Effect of Food

No clinically significant differences in fezolinetant pharmacokinetics were observed following administration with a high-calorie, high-fat meal containing approximately 1000 calories (500-600 calories from fat, 250 calories from carbohydrates, and 150 calories from protein).

Distribution

The mean apparent volume of distribution (Vz/F) of fezolinetant is 189 L. The plasma protein binding of fezolinetant is 51%. The blood-to-plasma ratio is 0.9.

Elimination

The effective half-life (t1/2) of fezolinetant is 9.6 hours in women with vasomotor symptoms. The apparent clearance at steady-state of fezolinetant is 10.8 L/h.

Metabolism

Fezolinetant is primarily metabolized by CYP1A2 and to a lesser extent by CYP2C9 and CYP2C19. A major metabolite of fezolinetant, ES259564, was identified in plasma. ES259564 is approximately 20-fold less potent than the parent. The metabolite-to-parent ratio ranges from 0.7 to 1.8.

Excretion

Following oral administration of fezolinetant, 76.9% of the dose was excreted in urine (1.1% unchanged) and 14.7% in feces (0.1% unchanged).

Specific Populations

There were no substantive differences in the pharmacokinetics of VEOZAH based on race and body weight (93 to 278 pounds).

Women with Renal Impairment

Following single-dose administration of 30 mg fezolinetant, there was no effect on VEOZAH exposure (Cmax and AUC) in women with mild (eGFR 60 to less than 90 mL/min/1.73 m^2) to severe (eGFR 15 to less than 30 mL/min/1.73 m^2) renal impairment. The AUC of ES259564 (a major metabolite of fezolinetant) in women with moderate (eGFR 30 to less than 60 mL/min/1.73 m^2) and severe (eGFR 15 to less than 30 mL/min/1.73 m^2) renal impairment increased by approximately 75% and 380%, respectively. VEOZAH has not been studied in individuals with end-stage renal disease (eGFR less than 15 mL/min/1.73 m^2).

Women with Hepatic Impairment

Following single-dose administration of 30 mg fezolinetant in women with mild Child-Pugh Class A cirrhosis, the mean Cmax increased by 23% and AUCinf increased by 56%, relative to women with normal hepatic function. In women with moderate Child-Pugh Class B cirrhosis, the mean Cmax of fezolinetant decreased by 15% and AUCinf increased by 96%. The Cmax of ES259564 decreased in both mild and moderate cirrhosis while AUCinf and AUClast increased less than 15%. VEOZAH has not been studied in individuals with severe Child-Pugh Class C cirrhosis.

Drug Interaction Studies

Clinical Studies and Model-Informed Approaches

Strong CYP1A2 Inhibitors: Fezolinetant Cmax increased by 80% and AUC increased by 840% following concomitant use with fluvoxamine (strong CYP1A2 inhibitor).

Moderate CYP1A2 Inhibitors: Fezolinetant Cmax increased by 40% and AUC increased by 360% following concomitant use with mexiletine (moderate CYP1A2 inhibitor) 400 mg every 8 hours.

Weak CYP1A2 Inhibitors: Fezolinetant Cmax increased by 30% and AUC increased by 100% following concomitant use with cimetidine (weak CYP1A2 inhibitor) 300 mg every 6 hours.

No clinically significant differences in fezolinetant exposure were observed in smokers (moderate CYP1A2 inducer).

In Vitro Studies

Cytochrome P450 (CYP) Enzymes: Fezolinetant and ES259564 are not inhibitors of CYP1A2, CYP2B6, CYP2C8, CYP2C9, CYP2C19, CYP2D6, and CYP3A4. Fezolinetant and ES259564 are not inducers of CYP1A2, CYP2B6, and CYP3A4.

Transporter Systems

Fezolinetant is not a substrate nor an inhibitor of P-glycoprotein (P-gp). ES259564 is a substrate of P-gp, but not an inhibitor of P-gp.

Both fezolinetant and ES259564 are not a substrate of BCRP, OATP1B1, and OATP1B3. In addition, ES259564 is not a substrate of OAT1, OAT3, OCT2, MATE1, and MATE2-K.

13 NONCLINICAL TOXICOLOGY

13.1 Carcinogenesis, Mutagenesis, Impairment of Fertility

Carcinogenesis

In a 2-year female rat carcinogenicity study and a 26-week carcinogenicity study in rasH2 transgenic mice, there was no evidence of drug-related carcinogenicity at 186-fold and 47-fold the human AUC24 at the human therapeutic dose of 45 mg, respectively.

Mutagenesis

Fezolinetant showed no genotoxic potential by the bacterial reverse mutation test, chromosomal aberration test, or in vivo micronucleus test.

Impairment of Fertility

Fezolinetant had no effect on female fertility or early embryonic development up to 100 mg/kg/day in rats (143-fold the human AUC24 at the human therapeutic dose). In the pre- and post-natal development study in rats, the F1 male showed incomplete balanopreputial separation at doses greater than or equal to 30 mg/kg/day (36-fold the human AUC24 at the human therapeutic dose), which delayed male reproductive maturation and affected fertility. These effects were not observed following dosing at 10 mg/kg/day (11-fold the human AUC24 at the human therapeutic dose) [see Use in Specific Populations (8.1)].

13.2 Animal Toxicology and/or Pharmacology

Repeat dose toxicity studies were conducted in intact female rats and cynomolgus monkeys. In female rats, daily administration of fezolinetant for 26 weeks at doses equal to or greater than 30 mg/kg/day (56-fold the human AUC24 at the human therapeutic dose) showed uterine atrophy and epithelial mucification of the vagina and cervix. In female cynomolgus monkeys, daily administration for 39 weeks at doses equal to or greater than 10 mg/kg/day (19-fold the human AUC24 at the human therapeutic dose) showed reduced ovarian activity.

14 CLINICAL STUDIES

14.1 Effects on Vasomotor Symptoms in Postmenopausal Women

The efficacy of VEOZAH for the treatment of moderate to severe vasomotor symptoms due to menopause was evaluated in the first 12-week, randomized, placebo-controlled, double-blind portion of each of two phase 3 clinical trials. In each of these two trials, after the first 12 weeks, women on placebo were then re-randomized to VEOZAH for a 40-week extension to evaluate safety for up to 52 weeks total exposure.

In Trials 1 (NCT04003155) and 2 (NCT04003142), 1022 women (522 in Trial 1 and 500 in Trial 2) who had a minimum average of 7 moderate to severe vasomotor symptoms per day were randomized to one of two doses of fezolinetant (including the 45 mg dosage strength) or placebo. Randomization was stratified by smoking status.

The mean age of the postmenopausal women was 54 years. Women self-identified as Caucasian (81%), African American (17%), Asian (1%), and Hispanic/Latina ethnicity (24%). The study population included menopausal women with one or more of the following: prior hysterectomy (32.1%), prior oophorectomy (21.6%), or prior hormone therapy use (19.9%). Those who were on prior hormone therapy underwent a wash-out period prior to trial participation.

The co-primary efficacy endpoints for both trials were the mean change from baseline in moderate to severe vasomotor symptoms frequency and severity to Weeks 4 and 12. Data from each trial demonstrated statistically significant and clinically meaningful (≥ 2 hot flashes over 24 hours) reduction from baseline in the frequency of moderate to severe vasomotor symptoms for VEOZAH 45 mg compared to placebo at Weeks 4 and 12. Data from each trial also demonstrated a statistically significant reduction from baseline in the severity of moderate to severe vasomotor symptoms (over 24 hours) at Weeks 4 and 12 for VEOZAH 45 mg compared to placebo.

Results of the co-primary endpoint for change from baseline to Weeks 4 and 12 in mean frequency of moderate to severe vasomotor symptoms over 24 hours from Trials 1 and 2 are shown in Table 2.

Table 2: Mean Baseline and Change from Baseline to Weeks 4 and 12 for Mean Frequency of Moderate to Severe Vasomotor Symptoms over 24 Hours in Women Treated with VEOZAH in Trials 1 and 2
Parameter | Trial 1 |  | Trial 2
Parameter | VEOZAH; 45 mg; (n=174) | Placebo; (n=175) | VEOZAH; 45 mg; (n=167) | Placebo; (n=167)
Baseline; Mean (SD) | 10.4 (3.92) | 10.5 (3.79) | 11.8 (8.26) | 11.6 (5.02)
Change from Baseline to Week 4; LS Mean (SE); Difference vs Placebo (95% CI); P-value | -5.4 (0.30); -2.1 (-2.9, -1.3); < 0.001 [Statistically significantly superior compared to placebo at the 0.05 level with multiplicity adjustment. LS Mean: Least Squares Mean estimated from a mixed model for repeated measures analysis of covariance; SD: Standard Deviation; SE: Standard Error.] | -3.3 (0.29); --; -- | -6.3 (0.33); -2.6 (-3.5, -1.6); < 0.001 | -3.7 (0.33); --; --
Change from Baseline to Week 12; LS Mean (SE); Difference vs Placebo (95% CI); P-value | -6.4 (0.31); -2.6 (-3.4, -1.7); < 0.001 | -3.9 (0.31); --; -- | -7.5 (0.39); -2.5 (-3.6, -1.5); < 0.001 | -5.0 (0.39); --; --

Results of the co-primary endpoint for change from baseline to Weeks 4 and 12 in mean severity of moderate to severe vasomotor symptoms over 24 hours from Trials 1 and 2 are shown in Table 3.

Table 3: Mean Baseline and Change from Baseline to Weeks 4 and 12 for Mean Severity of Moderate to Severe Vasomotor Symptoms over 24 Hours in Women Treated with VEOZAH in Trials 1 and 2
Parameter | Trial 1 |  | Trial 2
Parameter | VEOZAH 45 mg (n=174) | Placebo (n=175) | VEOZAH 45 mg (n=167) | Placebo (n=167)
Baseline; Mean (SD) | 2.4 (0.35) | 2.4 (0.35) | 2.4 (0.34) | 2.4 (0.32)
Change from Baseline to Week 4; LS Mean (SE); Difference vs Placebo (95% CI); P-value | -0.5 (0.04); -0.2 (-0.3, -0.1); 0.002 [Statistically significantly superior compared to placebo at the 0.05 level with multiplicity adjustment. LS Mean: Least Squares Mean estimated from a mixed model for repeated measures analysis of covariance; SD: Standard Deviation; SE: Standard Error.] | -0.3 (0.04); --; -- | -0.6 (0.05); -0.3 (-0.4, -0.2); < 0.001 | -0.3 (0.05); --; --
Change from Baseline to Week 12; LS Mean (SE); Difference vs Placebo (95% CI); P-value | -0.6 (0.05); -0.2 (-0.4, -0.1); 0.007 | -0.4 (0.05); --; -- | -0.8 (0.06); -0.3 (-0.5, -0.1); < 0.001 | -0.5 (0.06); --; --

14.2 Effects on Endometrium in Postmenopausal Women

In the VEOZAH 45 mg dose group across Trials 1, 2, and 3, endometrial biopsy assessments identified one case of endometrial hyperplasia and one case of endometrial malignancy. The rate of these events in the VEOZAH 45 mg dose group was ≤ 1% with the upper bound of the one-sided 95% confidence limit being ≤ 4%.

Table 4: Incidence of Endometrial Hyperplasia or Carcinoma after 12 Months of Treatment in Trials 1, 2, and 3
Final Diagnosis | VEOZAH; 45 mg; (n=350) | Placebo; (n=186)
Endometrial Hyperplasia and Carcinoma, n (%); One-sided upper limit of 95% CI; - Simple hyperplasia without atypia; - Endometrial adenocarcinoma | 2 (0.6%); 1.8%; 1; 1 | 0; 1.6%; 0; 0

Five cases of disordered proliferative endometrium were reported in women receiving VEOZAH 45 mg and four cases were reported in women receiving placebo across the three clinical trials. The EAIR was 1.4 per 100 person-years in VEOZAH 45 mg versus 2.0 per 100 person-years in the placebo group.

16 HOW SUPPLIED/STORAGE AND HANDLING

16.1 How Supplied

VEOZAH (fezolinetant) 45 mg tablets are supplied as round, light red, film-coated tablets, debossed with the Astellas logo and ‘645’ on the same side. VEOZAH tablets are available in the following package sizes:

- Bottles of 30 tablets with child resistant closure and desiccant, (NDC 0469-2660-30)
- Bottles of 90 tablets with child resistant closure and desiccant, (NDC 0469-2660-90)

16.2 Storage and Handling

Store at 20°C to 25°C (68°F to 77°F) with excursions permitted from 15°C to 30°C (59°F to 86°F) [see USP Controlled Room Temperature].

17 PATIENT COUNSELING INFORMATION

Advise patients to read the FDA-approved patient labeling (Patient Information).

Evaluation of Hepatic Injury During Treatment with VEOZAH

Inform patients that they will have to have a blood test to evaluate their liver function before beginning VEOZAH and while using VEOZAH monthly for the first 3 months, at 6 months, and 9 months after initialization of therapy. Advise patients to discontinue VEOZAH immediately and seek medical attention including hepatic laboratory tests if they experience signs or symptoms that may suggest liver abnormalities such as new onset fatigue, decreased appetite, nausea, vomiting, pruritus, jaundice, pale feces, dark urine, or abdominal pain [see Warnings and Precautions (5.1)].

Serious Adverse Reactions with VEOZAH

Inform patients of possible serious adverse reactions of VEOZAH including hepatic transaminase elevation and liver injury [see Warnings and Precautions (5.1)].

Common Adverse Reactions with VEOZAH

Inform patients of possible less serious but common adverse reactions of VEOZAH including abdominal pain, diarrhea, insomnia, back pain, and hot flush [see Adverse Reactions (6.1)].

Drug Interactions

Advise patients to report their use of any other prescription or nonprescription medications or dietary supplements [see Drug Interactions (7.1)].

Distributed by:

Astellas Pharma US, Inc.

Northbrook, IL 60062

© 2024 Astellas Pharma US, Inc. or its affiliates

432095-VEO-USA

PATIENT INFORMATION

VEOZAH® (vee-O-zah)

(fezolinetant)

tablets, for oral use

What is the most important information I should know about VEOZAH?

VEOZAH can cause serious side effects, including:

- Liver Problems. Your healthcare provider will do a blood test to check your liver before you start taking VEOZAH. Your healthcare provider will also do this blood test monthly for the first 3 months, at month 6, and month 9 after you start taking VEOZAH or if you have signs or symptoms that suggest liver problems. If your liver blood test values are elevated, your healthcare provider may advise you to stop treatment or request additional liver blood tests.

Stop VEOZAH right away and call your healthcare provider if you have the following signs or symptoms of liver problems:

- feeling more tired than you do usually
- decreased appetite
- nausea
- vomiting
- itching

- yellowing of the eyes or skin (jaundice)
- pale feces
- dark urine
- pain in the stomach (abdomen)

See “What are the possible side effects of VEOZAH?” for more information about side effects.

What is VEOZAH?

VEOZAH is a prescription medicine used to reduce moderate to severe vasomotor symptoms due to menopause. VEOZAH is not a hormone. Vasomotor symptoms are the feelings of warmth in the face, neck, and chest, or sudden intense feelings of heat and sweating (“hot flashes” or “hot flushes”).

Do not use VEOZAH if you:

- have cirrhosis.
- have severe kidney problems or kidney failure.
- are taking certain medicines called CYP1A2 inhibitors. Ask your healthcare provider if you are not sure.

Before you use VEOZAH, tell your healthcare provider about all of your medical conditions, including if you:

- have liver disease or liver problems.
- have kidney problems.
- have any medical conditions that may become worse while you are using VEOZAH.

Tell your healthcare provider about all the medicines you take, including prescription and over-the-counter medicines, vitamins, and herbal supplements. VEOZAH may affect the way other medicines work, and other medicines may affect how VEOZAH works. Keep a list of your medicines and show it to your healthcare provider and pharmacist when you get a new medicine.

How should I take VEOZAH?

- Take VEOZAH exactly as your healthcare provider tells you to take it.
- Take 1 VEOZAH tablet by mouth with or without food at about the same time each day.
- Swallow the VEOZAH tablet whole with liquid. Do not cut, crush, or chew the tablet.
- If you miss a dose of VEOZAH, take the missed dose as soon as possible on the same day, with at least 12 hours before the next scheduled dose. Return to your normal schedule the following day.

What are the possible side effects of VEOZAH?

VEOZAH can cause serious side effects, including:

- See “What is the most important information I should know about VEOZAH?”

Common side effects of VEOZAH include:

- stomach (abdominal) pain
- diarrhea
- difficulty sleeping (insomnia)
- back pain
- hot flashes or hot flushes

Tell your healthcare provider if you have any side effect that bothers you or does not go away.

These are not all the possible side effects of VEOZAH.

Call your doctor for medical advice about side effects. You may report side effects to FDA at 1-800-FDA-1088.

How should I store VEOZAH?

- Store VEOZAH at room temperature between 68°F to 77°F (20°C to 25°C).
- Dispose of the unused medicine through a take-back option, if available. See www.fda.gov/drugdisposal for more information.
- Keep VEOZAH and all medicines out of the reach of children.

General information about the safe and effective use of VEOZAH.

Medicines are sometimes prescribed for purposes other than those listed in a Patient Information leaflet. Do not use VEOZAH for a condition for which it was not prescribed. Do not give VEOZAH to other people, even if they have the same symptoms you have. It may harm them.

This Patient Information leaflet summarizes the most important information about VEOZAH. If you would like more information, talk with your healthcare provider. You can ask your pharmacist or healthcare provider for information about VEOZAH that is written for healthcare professionals.

What are the ingredients in VEOZAH?

Active ingredient: fezolinetant

Inactive ingredients: ferric oxide, hydroxypropyl cellulose, hypromellose, low-substituted hydroxypropyl cellulose, magnesium stearate, mannitol, microcrystalline cellulose, polyethylene glycol, talc, and titanium dioxide

Distributed by:

Astellas Pharma US, Inc.

Northbrook, IL 60062

© 2024 Astellas Pharma US, Inc. or its affiliates

432095-VEO-USA

For more information, go to www.VEOZAH.com or call 1-800-727-7003.

This Patient Information has been approved by the U.S. Food and Drug Administration. Revised: 12/2024

Package/Label Display Panel – VEOZAH Bottle Carton Label

NDC 0469-2660-30
Rx Only

VEOZAH®
(fezolinetant) tablets
45 mg

30 tablets

Package/Label Display Panel – VEOZAH Sample Bottle Carton Label

NDC 0469-2460-07

PROFESSIONAL SAMPLE-NOT FOR SALE

Rx Only

VEOZAH®
(fezolinetant) tablets
45 mg

7 tablets

Package/Label Display Panel- VEOZAH Sample Blister Carton Label

NDC 0469-2760-07

PROFESSIONAL SAMPLE-NOT FOR SALE

Rx Only

VEOZAH®
(fezolinetant) tablets
45 mg

7 tablets